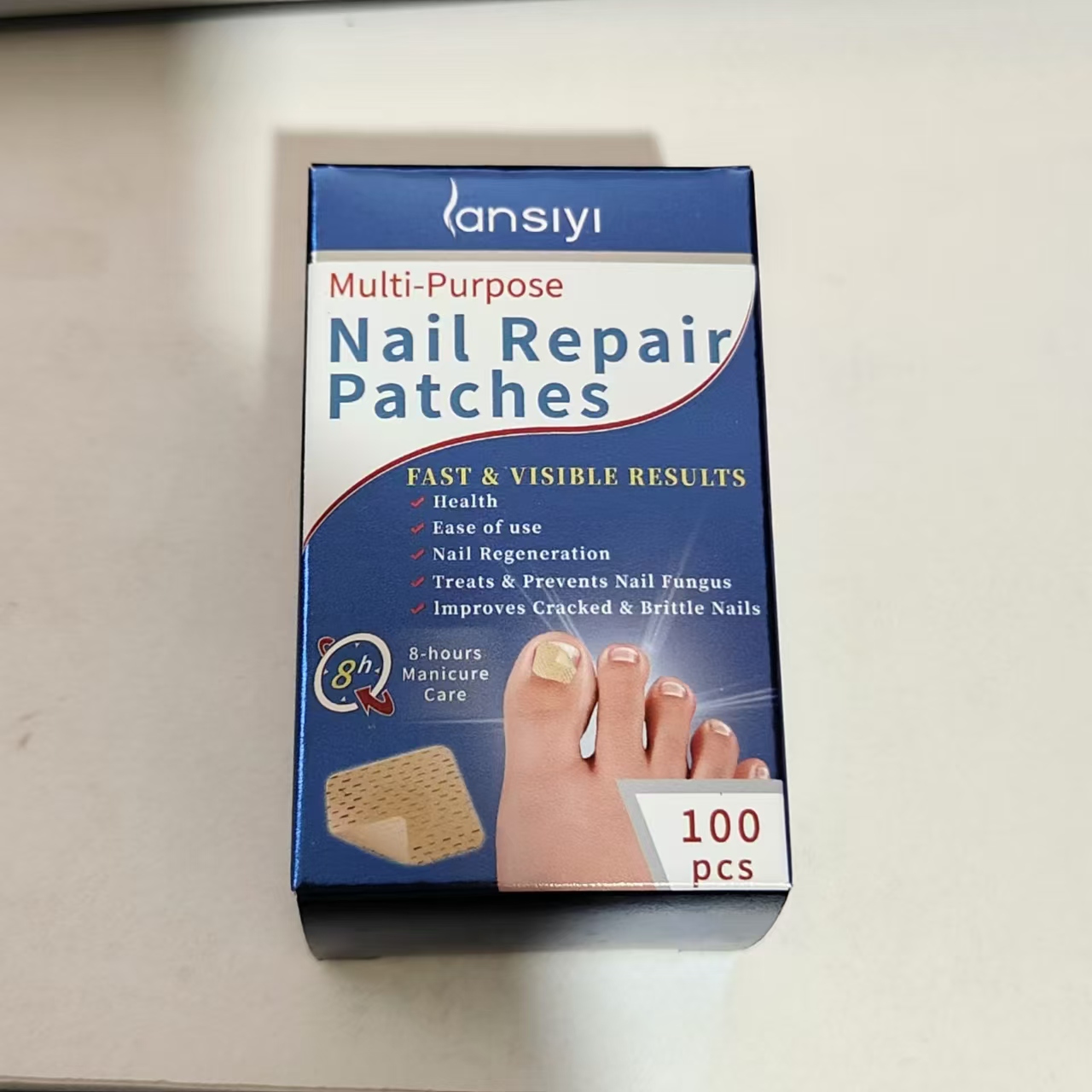 DRUG LABEL: Nail Repair Patches
NDC: 84727-001 | Form: OINTMENT
Manufacturer: Guangzhou Baishili Trading Co., Ltd
Category: otc | Type: HUMAN OTC DRUG LABEL
Date: 20240914

ACTIVE INGREDIENTS: TEA TREE OIL 100 mg/5 g; GARLIC 1000 mg/5 g; ALLANTOIN 1000 mg/5 g
INACTIVE INGREDIENTS: GLYCERIN 100 mg/5 g

Active ingredients

Tea tree oil 20%

Allantoin 5%

Garlic Extract 0.8%

Usage

Remove the protective paper from thepatch and apply it to the affected area by pressingfirmly.

Uses

Remove the protective paper from thepatch and apply it to the affected area by pressingfirmly.

Warning

External and personal use only- do notshare.Avoid contact with eyes. lf irritation occurs.discontinue use.Do not use if you are hyperse-nsitive to any of the ingredients.

Warning

External and personal use only- do notshare.Avoid contact with eyes. lf irritation occurs,discontinue use.Do not use if you are hyperse-nsitive to any of the ingredients.

Warning

External and personal use only- do notshare.Avoid contact with eyes. lf irritation occurs.discontinue use.Do not use if you are hyperse-nsitive to any of the ingredients.

Warning

External and personal use only- do notshare.Avoid contact with eyes.lf irritation occursdiscontinue use.Do not use if you are hyperse.nsitive to any of the ingredients.

Keep out of reach of children.

if swallowed, get medical help or contact a Poison Control Center right away.

DOSAGE & ADMINISTRATION SECTION

Use one piece for each nail, and apply for 8 hours each time

Inactive Ingredients

Glycerin, Kochia, Conidium